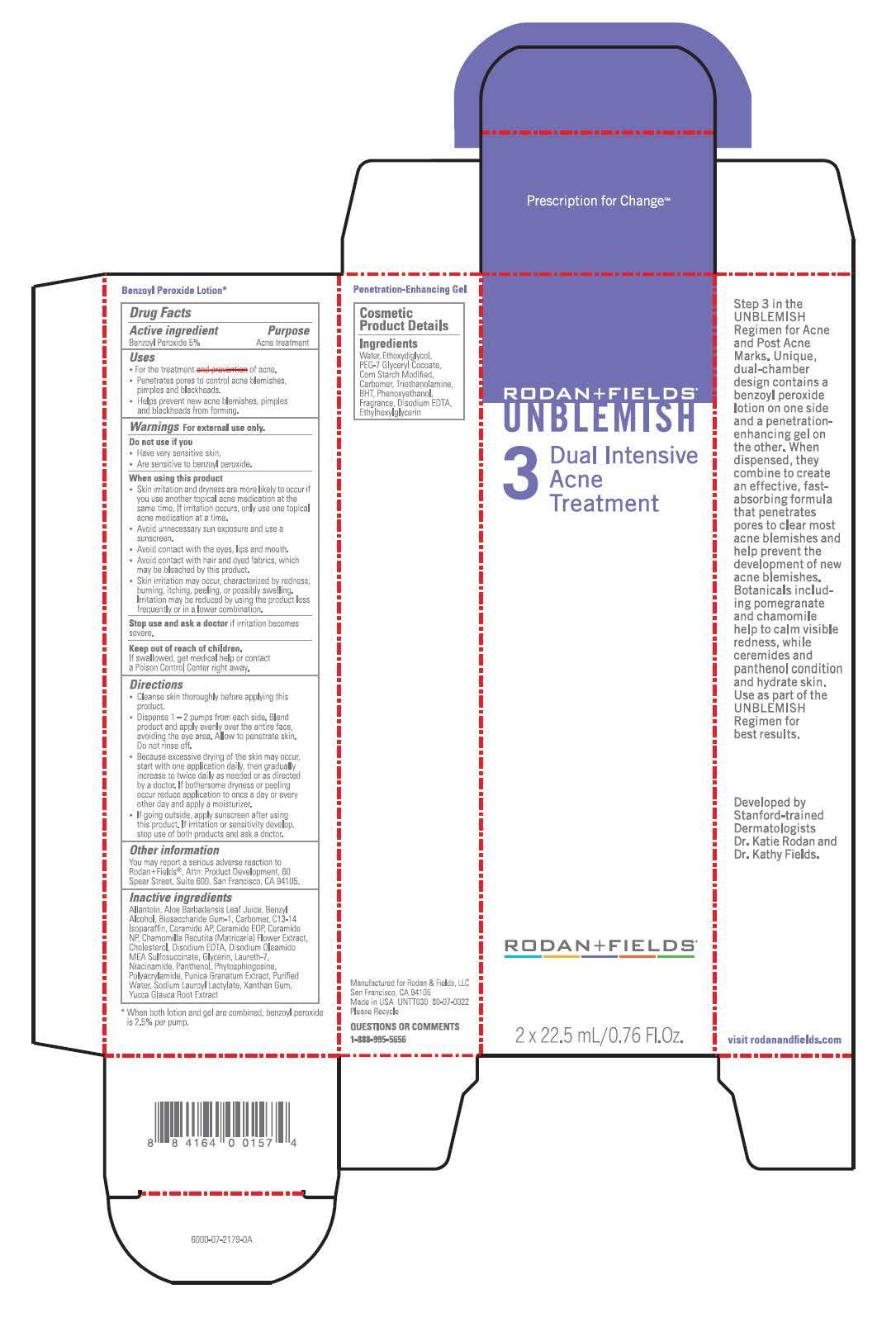 DRUG LABEL: Unblemish
NDC: 14222-2000 | Form: LOTION
Manufacturer: Rodan & Fields, LLC
Category: otc | Type: HUMAN OTC DRUG LABEL
Date: 20140228

ACTIVE INGREDIENTS: BENZOYL PEROXIDE 50 mg/1 mL
INACTIVE INGREDIENTS: ALLANTOIN; ALOE VERA LEAF; BENZYL ALCOHOL; BIOSACCHARIDE GUM-1; CARBOMER 934; C13-14 ISOPARAFFIN; CERAMIDE 6 II; CERAMIDE 1; CERAMIDE 3; CHAMOMILE; CHOLESTEROL; EDETATE DISODIUM; DISODIUM OLEAMIDO MEA-SULFOSUCCINATE; GLYCERIN; LAURETH-7; NIACINAMIDE; PANTHENOL; PHYTOSPHINGOSINE; SODIUM ACRYLOYLDIMETHYLTAURATE-ACRYLAMIDE COPOLYMER (1:1; 90000-150000 MPA.S); PUNICA GRANATUM ROOT BARK; WATER; SODIUM LAUROYL LACTYLATE; XANTHAN GUM; YUCCA GLAUCA ROOT

Rodan + Fields Unblemish

Active ingredient

Benzoyl Peroxide 5%

Purpose

Acne treatment

Uses

- For the treatment of acne.
- Penetrates pores to control acne blemishes, pimples and blackheads.
- Helps prevent new acne blemishes, pimples and blackheads from forming.

Warnings

For external use only.

Do not use if you

- Have very sensitive skin.
- Are sensitive to benzoyl peroxide.

When using this product

- Skin irritation and dryness are more likely to occur if you use another topical acne medication at the same time. If irritation occurs, only use one topical acne medication at a time.
- Avoid unnecessary sun exposure and use a sunscreen.
- Avoid contact with the eyes, lips and mouth.
- Avoid contact with hair and dyed fabrics, which may be bleached by this product.
- Skin irritation may occur, characterized by redness, burning, itching, peeling, or possibly swelling. Irritation may be reduced by using the product less frequently or in a lower combination.

Stop use and ask a doctor if irritation becomes severe.

Keep out of reach of children.

If swallowed, get medical help or contact a Poison Control Center right away.

Directions

- Cleanse skin thoroughly before applying this product.
- Dispense 1-2 pumps from each side. Blend product and apply evenly over the entire face, avoiding the eye area. Allow to penetrate skin. Do not rinse off.
- Because excessive drying of the skin may occur, start with one application daily, then gradually increase to twice daily as needed or as directed by a doctor. If bothersome dryness or peeling occur reduce application to once a day or every other day and apply a moisturizer.
- If going outside, apply sunscreen after using this product. If irritation or sensitivity develop, stop use of both products and ask a doctor.

Other information

You may report a serious adverse reaction to Rodan+Fields®, Attn: Product Development, 60 Spear Street, Suite 600, San Francisco, CA 94105.

Inactive ingredients

Allantoin, Aloe Barbadensis Leaf Juice, Benzyl Alcohol, Biosaccharide Gum-1, Carbomer, C13-14 Isoparaffin, Ceramide AP, Ceramide EOP, Ceramide NP, Chamomilla Recutita (Matricaria) Flower Extract, Cholesterol, Disodium EDTA, Disodium Oleamido MEA Sulfosuccinate, Glycerin, Laureth-7, Niacinamide, Panthenol, Phytosphingosine, Polyacrylamide, Punica Granatum Extract, Purified Water, Sodium Lauroyl Lactylate, Xanthan Gum, Yucca Glauca Root Extract

Principal Display Panel - Rodan+Fields

Rodan+Fields

Unblemish

Dual Intensive Acne Treatment

2 X 22.5 mL/0.76 Fl. Oz.